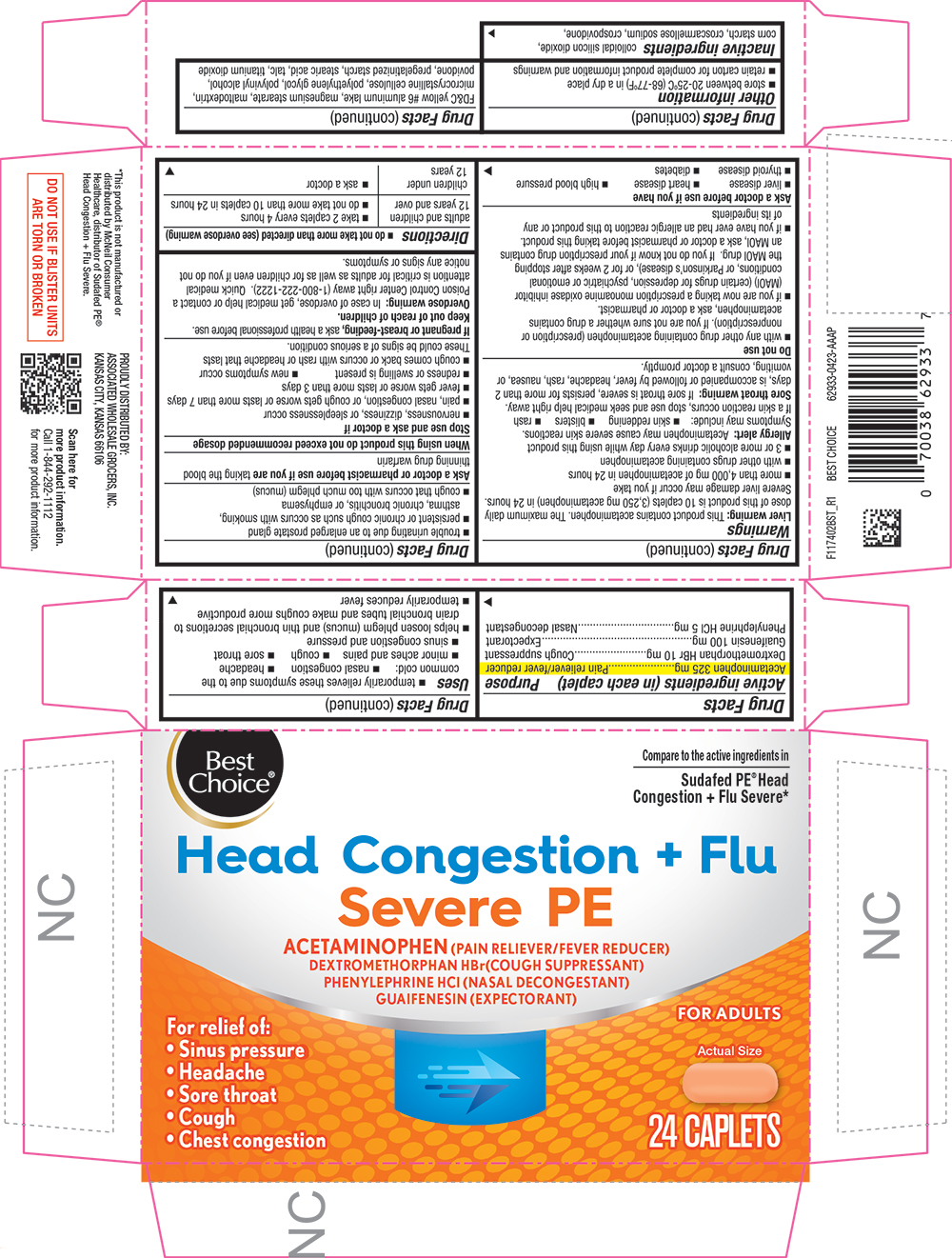 DRUG LABEL: Head Congestion plus Flu Severe PE
NDC: 63941-274 | Form: TABLET, COATED
Manufacturer: VALU MERCHANDISERS COMPANY
Category: otc | Type: HUMAN OTC DRUG LABEL
Date: 20251211

ACTIVE INGREDIENTS: ACETAMINOPHEN 325 mg/1 1; DEXTROMETHORPHAN HYDROBROMIDE 10 mg/1 1; GUAIFENESIN 100 mg/1 1; PHENYLEPHRINE HYDROCHLORIDE 5 mg/1 1
INACTIVE INGREDIENTS: STEARIC ACID; STARCH, PREGELATINIZED CORN; TALC; TITANIUM DIOXIDE; SILICON DIOXIDE; CROSCARMELLOSE SODIUM; CROSPOVIDONE, UNSPECIFIED; FD&C YELLOW NO. 6; ALUMINUM OXIDE; MAGNESIUM STEARATE; MALTODEXTRIN; CELLULOSE, MICROCRYSTALLINE; POLYETHYLENE GLYCOL, UNSPECIFIED; POLYVINYL ALCOHOL, UNSPECIFIED; POVIDONE, UNSPECIFIED

1174-BST-2023-0414

Drug Facts

ACTIVE INGREDIENT

PURPOSE

Active ingredients (in each caplet) | Purposes
Acetaminophen 325 mg | Pain reliever/fever reducer
Dextromethorphan HBr 10 mg | Cough suppressant
Guaifenesin 100 mg | Expectorant
Phenylephrine HCl 5 mg | Nasal decongestant

Uses

- temporarily relieves these symptoms due to the common cold:
  - nasal congestion
  - headache
  - minor aches and pains
  - cough
  - sore throat
  - sinus congestion and pressure
- helps loosen phlegm (mucus) and thin bronchial secretions to drain bronchial tubes and make coughs more productive
- temporarily reduces fever

Warnings

Liver warning

This product contains acetaminophen. The maximum daily dose of this product is 10 caplets (3,250 mg acetaminophen) in 24 hours. Severe liver damage may occur if you take

- more than 4,000 mg of acetaminophen in 24 hours
- with other drugs containing acetaminophen
- 3 or more alcoholic drinks every day while using this product

Allergy alert

Acetaminophen may cause severe skin reactions. Symptoms may include:

- skin reddening
- blisters
- rash

If a skin reaction occurs, stop use and seek medical help right away.

Sore throat warning

If sore throat is severe, persists for more than 2 days, is accompanied or followed by fever, headache, rash, nausea, or vomiting, consult a doctor promptly.

Do not use

- with any other drug containing acetaminophen (prescription or nonprescription). If you are not sure whether a drug contains acetaminophen, ask a doctor or pharmacist.
- if you are now taking a prescription monoamine oxidase inhibitor (MAOI) (certain drugs for depression, psychiatric, or emotional conditions, or Parkinson's disease), or for 2 weeks after stopping the MAOI drug. If you do not know if your prescription drug contains an MAOI, ask a doctor or pharmacist before taking this product.
- if you have ever had an allergic reaction to this product or any of its ingredients

Ask a doctor before use if you have

- liver disease
- heart disease
- high blood pressure
- thyroid disease
- diabetes
- trouble urinating due to an enlarged prostate gland
- persistent or chronic cough such as occurs with smoking, asthma, chronic bronchitis, or emphysema
- cough that occurs with too much phlegm (mucus)

Ask a doctor or pharmacist before use if you are taking the blood thinning drug warfarin

When using this product do not exceed recommended dosage

Stop use and ask a doctor if

- nervousness, dizziness, or sleeplessness occur
- pain, nasal congestion, or cough gets worse or lasts more than 7 days
- fever gets worse or lasts more than 3 days
- redness or swelling is present
- new symptoms occur
- cough comes back or occurs with rash or headache that lasts

These could be signs of a serious condition.

PREGNANCY OR BREAST FEEDING

If pregnant or breast-feeding, ask a health professional before use.

Keep out of reach of children.

Overdose warning

In case of overdose, get medical help or contact a Poison Control Center right away (1-800-222-1222). Quick medical attention is critical for adults as well as for children even if you do not notice any signs or symptoms.

Directions

- do not take more than directed (see overdose warning)

adults and children 12 years and over | - take 2 caplets every 4 hours - do not take more than 10 caplets in 24 hours
children under 12 years | - ask a doctor

Other information

- store between 20-25°C (68-77°F) in a dry place
- retain carton for complete product information and warnings

Inactive ingredients

colloidal silicon dioxide, corn starch, croscarmellose sodium, crospovidone, FD&C yellow #6 aluminum lake, magnesium stearate, maltodextrin, microcrystalline cellulose, polyethylene glycol, polyvinyl alcohol, povidone, pregelatinized starch, stearic acid, talc, titanium dioxide

PRINCIPAL DISPLAY PANEL

Best Choice®

Compare to the active ingredients in Sudafed PE® Head Congestion + Flu Severe*

Head Congestion + Flu Severe PE

ACETAMINOPHEN (PAIN RELIEVER/FEVER REDUCER)

DEXTROMETHORPHAN HBr (COUGH SUPPRESSANT)

PHENYLEPHRINE HCl (NASAL DECONGESTION)

GAUIFENESIN (EXPECTORANT)

For relief of:

• Sinus pressure

• Headache

• Sore throat

• Cough

• Chest congestion

FOR ADULTS

Actual Size

24 CAPLETS